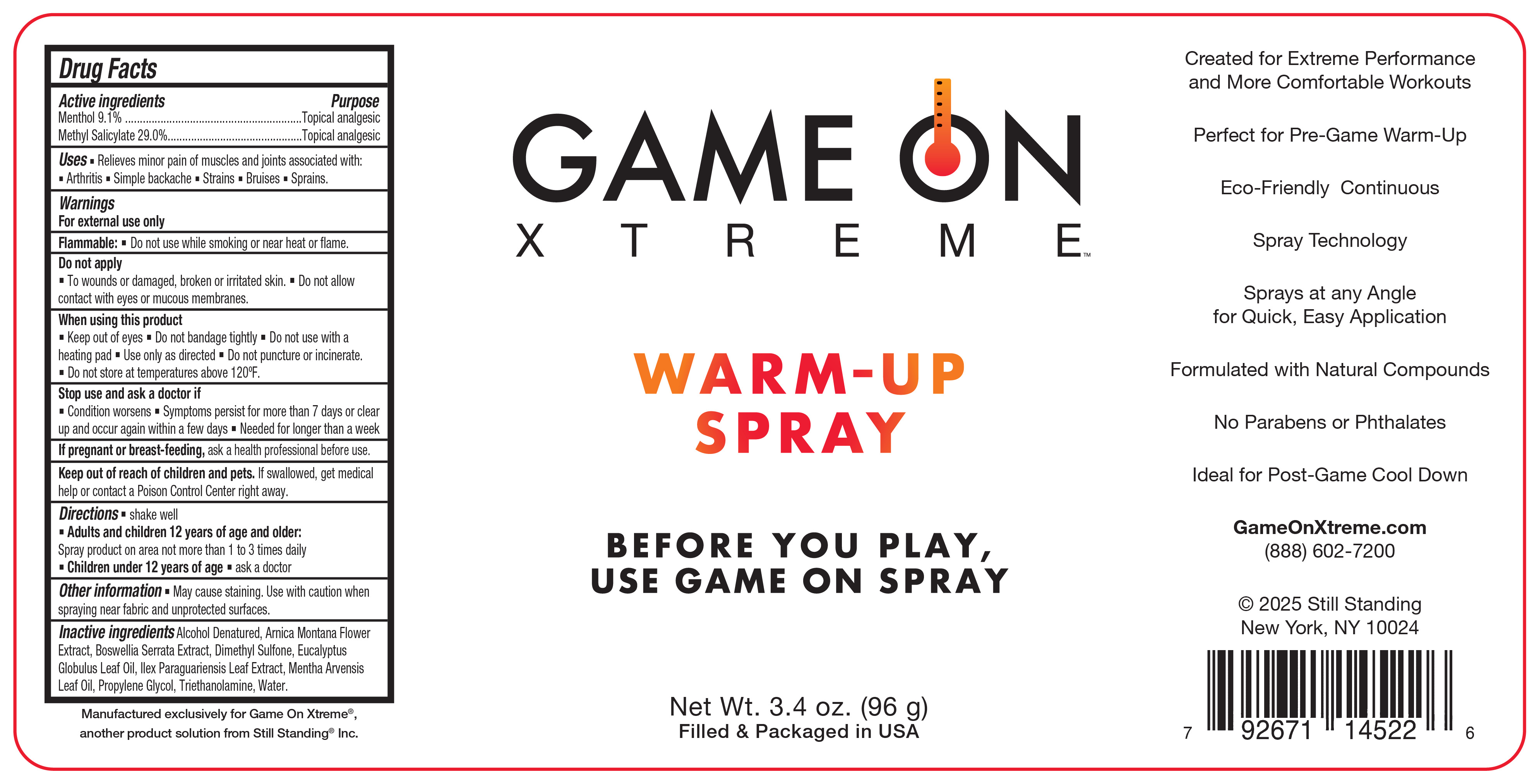 DRUG LABEL: Game On
NDC: 66902-378 | Form: SPRAY
Manufacturer: Natural Essentials, Inc.
Category: otc | Type: HUMAN OTC DRUG LABEL
Date: 20250820

ACTIVE INGREDIENTS: MENTHOL, UNSPECIFIED FORM 91 mg/1 g; METHYL SALICYLATE 290 mg/1 g
INACTIVE INGREDIENTS: BOSWELLIA SERRATA WHOLE; DIMETHYL SULFONE; EUCALYPTUS GLOBULUS LEAF OIL; MENTHA ARVENSIS LEAF OIL; ARNICA MONTANA FLOWER; ALCOHOL; PROPYLENE GLYCOL; WATER; TROLAMINE; ILEX PARAGUARIENSIS LEAF

Active ingredients

Menthol 9.1%

Methyl Salicylate 29.0%

Purpose

Topical analgesic

Uses

Relieves minor pain of muscles and joints associated with:

- Arthritis
- Simple backache
- Strains
- Bruises
- Sprains

Warnings

For external use only

Do not apply

- to wounds or damaged, broken, or irritated skin.
- Do not allow contact with eyes or mucous membranes

When using this product

- Keep out of eyes
- Do not bandage tightly
- Do not use with a heating pad
- Use only as directed
- Do not puncture or incinerate
- Do not sotre at temperatures above 120°F

Stop use and ask a doctor if

- Condition worsens
- Symptoms persist for more than 7 days or clear up and occur again within a few days
- Needed for longer than a week

If pregnant or breast-feeding,

ask a health professional before use.

Keep out of reach of children and pets.

If swallowed, get medical help or contact a Poison Control Center right away.

Directions

- shake well
- Adults and children 12 years of age and older: Spray product on area not more than 1 to 3 times daily
- Children under 12 years of age: Ask a doctor

Other information

- May cause staining. Use with caution when spraying near fabric and unprotected surfaces.

Inactive ingredients

Alcohol Denatured, Arnica Montana Flower Extract, Boswellia Serrata Extract, Dimethyl Sulfone, Eucalyptus Globulus Leaf Oil, Ilex Paraguariensis Leaf Extract, Mentha Arvensis Leaf Oil, Propylene Glycol, Treithanolamine, Water

Principal Display Panel - 96 g Label

GAME ON

XTREME

Warm-up

Spray

BEFORE YOU PLAY,

USE GAME ON SPRAY

Net Wt. 3.4 oz (96 g)

Filled & Packaged in USA